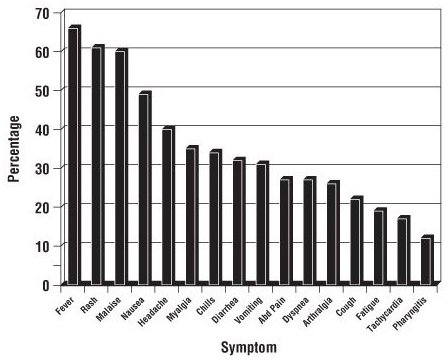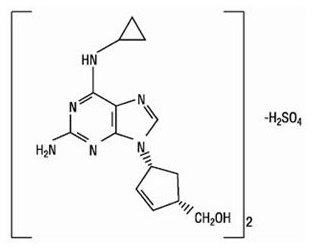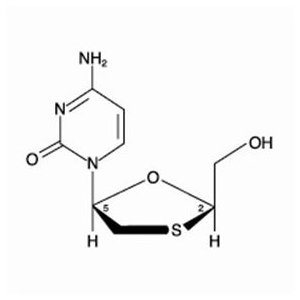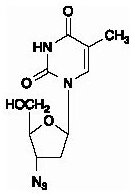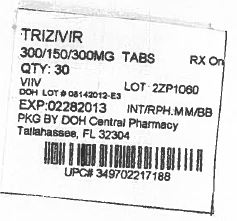 DRUG LABEL: TRIZIVIR
NDC: 53808-0990 | Form: TABLET, FILM COATED
Manufacturer: State of Florida DOH Central Pharmacy
Category: prescription | Type: HUMAN PRESCRIPTION DRUG LABEL
Date: 20140424

ACTIVE INGREDIENTS: ABACAVIR SULFATE 300 mg/1 1; LAMIVUDINE 150 mg/1 1; ZIDOVUDINE 300 mg/1 1
INACTIVE INGREDIENTS: MAGNESIUM STEARATE; CELLULOSE, MICROCRYSTALLINE; SODIUM STARCH GLYCOLATE TYPE A POTATO; FD&C BLUE NO. 2; HYPROMELLOSES; POLYETHYLENE GLYCOLS; TITANIUM DIOXIDE; FERRIC OXIDE YELLOW

HIGHLIGHTS OF PRESCRIBING INFORMATION

These highlights do not include all the information needed to use TRIZIVIR safely and effectively. See full prescribing information for TRIZIVIR.
TRIZIVIR (abacavir sulfate, lamivudine, and zidovudine) Tablets, for oral use
Initial U.S. Approval: 2000

WARNING: RISK OF HYPERSENSITIVITY REACTIONS, HEMATOLOGIC TOXICITY, MYOPATHY, LACTIC ACIDOSIS AND SEVERE HEPATOMEGALY, EXACERBATIONS OF HEPATITIS B

See full prescribing information for complete boxed warning.

- Serious and sometimes fatal hypersensitivity reactions have been associated with abacavir-containing products. (5.1)
- Hypersensitivity to abacavir is a multi-organ clinical syndrome. (5.1)
- Patients who carry the HLA-B*5701 allele are at high risk for experiencing a hypersensitivity reaction to abacavir. (5.1)
- Discontinue TRIZIVIR as soon as a hypersensitivity reaction is suspected. Regardless of HLA-B*5701 status, permanently discontinue TRIZIVIR if hypersensitivity cannot be ruled out. (5.1)
- Following a hypersensitivity reaction to abacavir, NEVER restart TRIZIVIR or any other abacavir-containing product. (5.1)
- Hematologic toxicity, including neutropenia and anemia, has been associated with the use of zidovudine, a component of TRIZIVIR. (5.2)
- Symptomatic myopathy associated with prolonged use of zidovudine. (5.3)
- Lactic acidosis and severe hepatomegaly with steatosis, including fatal cases, have been reported with the use of nucleoside analogues. (5.4)
- Severe acute exacerbations of hepatitis B have been reported in patients who are co-infected with hepatitis B virus (HBV) and human immunodeficiency virus (HIV-1) and have discontinued lamivudine, a component of TRIZIVIR. Monitor hepatic function closely in these patients and, if appropriate, initiate anti-hepatitis B treatment. (5.5)

1 INDICATIONS AND USAGE

TRIZIVIR, a combination of abacavir, lamivudine, and zidovudine, each nucleoside analogue HIV-1 reverse transcriptase inhibitors, is indicated in combination with other antiretroviral agents for the treatment of HIV-1 infection. (1)

2 DOSAGE AND ADMINISTRATION

- A medication guide and warning card should be dispensed with each new prescription and refill. (2)
- Adults and Adolescents: 1 tablet twice daily. (2.1)
- Not recommended in adolescents who weigh less than 40 kg. (2.1)
- Do not prescribe for patients requiring dosage adjustment or patients with hepatic impairment. (2.2)

3 DOSAGE FORMS AND STRENGTHS

Tablets contain 300 mg abacavir, 150 mg of lamivudine, and 300 mg of zidovudine. (3)

4 CONTRAINDICATIONS

- Previously demonstrated hypersensitivity to abacavir or any other component of the product. (4, 5.1, 6)
- Hepatic impairment. (4)

WARNINGS AND PRECAUTIONS

- See boxed warning for information about the following: hypersensitivity reactions, hematologic toxicity, myopathy, lactic acidosis and severe hepatomegaly, and severe acute exacerbations of hepatitis B. (5.1, 5.2, 5.3, 5.4, 5.5)
- Hepatic decompensation, some fatal, has occurred in HIV-1/HCV co-infected patients receiving combination antiretroviral therapy and interferon alfa with or without ribavirin. Discontinue TRIZIVIR as medically appropriate and consider dose reduction or discontinuation of interferon alfa, ribavirin, or both. (5.6)
- Exacerbation of anemia has been reported in HIV-1/HCV co-infected patients receiving ribavirin and zidovudine. Coadministration of ribavirin and zidovudine is not advised. (5.6)
- Immune reconstitution syndrome (5.7) and redistribution/accumulation of body fat (5.8) have been reported in patients treated with combination antiretroviral therapy.
- TRIZIVIR should not be administered with other products containing abacavir, lamivudine, or zidovudine; or with emtricitabine. (5.11)

6 ADVERSE REACTIONS

The most commonly reported adverse reactions (incidence ≥10%) in clinical trials were nausea, headache, malaise and fatigue, and nausea and vomiting. (6.1)

To report SUSPECTED ADVERSE REACTIONS, contact ViiV Healthcare at 1-877-844-8872 or FDA at 1-800-FDA-1088 or www.fda.gov/medwatch.

7 DRUG INTERACTIONS

- Concomitant use with the following drugs should be avoided: stavudine (7.1), doxorubicin (7.2).
- Ethanol: Decreases the elimination of abacavir. (7.3)
- Bone marrow suppressive/cytotoxic agents: May increase the hematologic toxicity of zidovudine. (7.4)
- Methadone: An increased methadone dose may be required in a small number of patients. (7.6)

FULL PRESCRIBING INFORMATION

WARNING: RISK OF HYPERSENSITIVITY REACTIONS, HEMATOLOGIC TOXICITY, MYOPATHY, LACTIC ACIDOSIS AND SEVERE HEPATOMEGALY, EXACERBATIONS OF HEPATITIS B

Hypersensitivity Reactions: Serious and sometimes fatal hypersensitivity reactions have been associated with abacavir sulfate, a component of TRIZIVIR. Hypersensitivity to abacavir is a multi-organ clinical syndrome usually characterized by a sign or symptom in 2 or more of the following groups: (1) fever, (2) rash, (3) gastrointestinal (including nausea, vomiting, diarrhea, or abdominal pain), (4) constitutional (including generalized malaise, fatigue, or achiness), and (5) respiratory (including dyspnea, cough, or pharyngitis). Discontinue TRIZIVIR as soon as a hypersensitivity reaction is suspected.

Patients who carry the HLA-B*5701 allele are at high risk for experiencing a hypersensitivity reaction to abacavir. Prior to initiating therapy with abacavir, screening for the HLA-B*5701 allele is recommended; this approach has been found to decrease the risk of hypersensitivity reaction. Screening is also recommended prior to reinitiation of abacavir in patients of unknown HLA-B*5701 status who have previously tolerated abacavir. HLA-B*5701-negative patients may develop a suspected hypersensitivity reaction to abacavir; however, this occurs significantly less frequently than in HLA-B*5701-positive patients.

Regardless of HLA-B*5701 status, permanently discontinue TRIZIVIR if hypersensitivity cannot be ruled out, even when other diagnoses are possible.

Following a hypersensitivity reaction to abacavir, NEVER restart TRIZIVIR or any other abacavir-containing product because more severe symptoms can occur within hours and may include life-threatening hypotension and death.

Reintroduction of TRIZIVIR or any other abacavir-containing product, even in patients who have no identified history or unrecognized symptoms of hypersensitivity to abacavir therapy, can result in serious or fatal hypersensitivity reactions. Such reactions can occur within hours [see Warnings and Precautions (5.1)].

Hematologic Toxicity: Zidovudine, a component of TRIZIVIR, has been associated with hematologic toxicity, including neutropenia and severe anemia, particularly in patients with advanced Human Immunodeficiency Virus (HIV-1) disease [see Warnings and Precautions (5.2)].

Myopathy: Prolonged use of zidovudine has been associated with symptomatic myopathy [see Warnings and Precautions (5.3)].

Lactic Acidosis and Severe Hepatomegaly: Lactic acidosis and severe hepatomegaly with steatosis, including fatal cases, have been reported with the use of nucleoside analogues alone or in combination, including abacavir, lamivudine, zidovudine, and other antiretrovirals [see Warnings and Precautions (5.4)].

Exacerbations of Hepatitis B: Severe acute exacerbations of hepatitis B have been reported in patients who are co-infected with hepatitis B virus (HBV) and HIV-1 and have discontinued lamivudine, which is one component of TRIZIVIR. Hepatic function should be monitored closely with both clinical and laboratory follow-up for at least several months in patients who discontinue TRIZIVIR and are co-infected with HIV-1 and HBV. If appropriate, initiation of anti-hepatitis B therapy may be warranted [see Warnings and Precautions (5.5)].

1 INDICATIONS AND USAGE

TRIZIVIR is indicated in combination with other antiretrovirals or alone for the treatment of HIV-1 infection.

Additional important information on the use of TRIZIVIR for treatment of HIV-1 infection:

- TRIZIVIR is one of multiple products containing abacavir. Before starting TRIZIVIR, review medical history for prior exposure to any abacavir-containing product in order to avoid reintroduction in a patient with a history of hypersensitivity to abacavir [see Warnings and Precautions (5.1), Adverse Reactions (6)].
- TRIZIVIR is a fixed-dose combination of 3 nucleoside analogues: abacavir, lamivudine, and zidovudine and is intended only for patients whose regimen would otherwise include these 3 components.
- Limited data exist on the use of TRIZIVIR alone in patients with higher baseline viral load levels (>100,000 copies/mL) [see Clinical Studies (14)].

2 DOSAGE AND ADMINISTRATION

- A Medication Guide and Warning Card that provide information about recognition of hypersensitivity reactions should be dispensed with each new prescription and refill.
- TRIZIVIR can be taken with or without food.

2.1 Adults and Adolescent Patients

The recommended oral dose of TRIZIVIR is one tablet twice daily.

TRIZIVIR is not recommended in adolescents who weigh less than 40 kg because it is a fixed-dose tablet and cannot be dose adjusted.

2.2 Dosage Adjustment

Because it is a fixed-dose combination, TRIZIVIR should not be prescribed for:

- patients requiring dosage adjustment such as those with creatinine clearance <50 mL/min.
- patients with hepatic impairment.

3 DOSAGE FORMS AND STRENGTHS

TRIZIVIR Tablets contain 300 mg of abacavir as abacavir sulfate, 150 mg of lamivudine, and 300 mg of zidovudine. The tablets are blue-green, capsule-shaped, film-coated, and imprinted with “GX LL1” on one side with no markings on the reverse side.

4 CONTRAINDICATIONS

TRIZIVIR Tablets are contraindicated in patients with:

- previously demonstrated hypersensitivity to abacavir or any other component of the product. NEVER restart TRIZIVIR or any other abacavir-containing product following a hypersensitivity reaction to abacavir, regardless of HLA-B*5701 status [see Warnings and Precautions (5.1), Adverse Reactions (6)].
- hepatic impairment [see Use in Specific Populations (8.7)].

WARNINGS AND PRECAUTIONS

5.1 Hypersensitivity Reaction

Serious and sometimes fatal hypersensitivity reactions have been associated with TRIZIVIR and other abacavir-containing products. Patients who carry the HLA-B*5701 allele are at high risk for experiencing a hypersensitivity reaction to abacavir. Prior to initiating therapy with abacavir, screening for the HLA-B*5701 allele is recommended; this approach has been found to decrease the risk of a hypersensitivity reaction. Screening is also recommended prior to reinitiation of abacavir in patients of unknown HLA-B*5701 status who have previously tolerated abacavir. For HLA-B*5701-positive patients, treatment with an abacavir-containing regimen is not recommended and should be considered only with close medical supervision and under exceptional circumstances when the potential benefit outweighs the risk.

HLA-B*5701-negative patients may develop a hypersensitivity reaction to abacavir; however, this occurs significantly less frequently than in HLA-B*5701-positive patients. Regardless of HLA-B*5701 status, permanently discontinue TRIZIVIR if hypersensitivity cannot be ruled out, even when other diagnoses are possible.

Important information on signs and symptoms of hypersensitivity, as well as clinical management, is presented below.

Signs and Symptoms of Hypersensitivity: Hypersensitivity to abacavir is a multi-organ clinical syndrome usually characterized by a sign or symptom in 2 or more of the following groups.

Group 1: Fever

Group 2: Rash

Group 3: Gastrointestinal (including nausea, vomiting, diarrhea, or abdominal pain)

Group 4: Constitutional (including generalized malaise, fatigue, or achiness)

Group 5: Respiratory (including dyspnea, cough, or pharyngitis)

Hypersensitivity to abacavir following the presentation of a single sign or symptom has been reported infrequently.

Hypersensitivity to abacavir was reported in approximately 8% of 2,670 subjects (n = 206) in 9 clinical trials (range: 2% to 9%) with enrollment from November 1999 to February 2002. Data on time to onset and symptoms of suspected hypersensitivity were collected on a detailed data collection module. The frequencies of symptoms are shown in Figure 1. Symptoms usually appeared within the first 6 weeks of treatment with abacavir, although the reaction may occur at any time during therapy. Median time to onset was 9 days; 89% appeared within the first 6 weeks; 95% of subjects reported symptoms from 2 or more of the 5 groups listed above.

A trial with ZIAGEN® (abacavir sulfate) used double-blind ascertainment of suspected hypersensitivity reactions. During the blinded portion of the trial, suspected hypersensitivity to abacavir was reported by investigators in 9% of 324 subjects in the abacavir group and 3% of 325 subjects in the zidovudine group.

Figure 1. Hypersensitivity-Related Symptoms Reported With ≥10% Frequency in Clinical Trials (n = 206 Subjects)

Other less common signs and symptoms of hypersensitivity include lethargy, myolysis, edema, abnormal chest x-ray findings (predominantly infiltrates, which can be localized), and paresthesia. Anaphylaxis, liver failure, renal failure, hypotension, adult respiratory distress syndrome, respiratory failure, and death have occurred in association with hypersensitivity reactions.

Physical findings associated with hypersensitivity to abacavir in some subjects include lymphadenopathy, mucous membrane lesions (conjunctivitis and mouth ulcerations), and rash. The rash usually appears maculopapular or urticarial, but may be variable in appearance. There have been reports of erythema multiforme. Hypersensitivity reactions have occurred without rash.

Laboratory abnormalities associated with hypersensitivity to abacavir in some subjects include elevated liver function tests, elevated creatinine phosphokinase, elevated creatinine, and lymphopenia.

Clinical Management of Hypersensitivity: Discontinue TRIZIVIR as soon as a hypersensitivity reaction is suspected. To minimize the risk of a life-threatening hypersensitivity reaction, permanently discontinue TRIZIVIR if hypersensitivity cannot be ruled out, even when other diagnoses are possible (e.g., acute onset respiratory diseases such as pneumonia, bronchitis, pharyngitis, or influenza; gastroenteritis; or reactions to other medications).

Following a hypersensitivity reaction to abacavir, NEVER restart TRIZIVIR or any other abacavir-containing product because more severe symptoms can occur within hours and may include life-threatening hypotension and death.

When therapy with TRIZIVIR has been discontinued for reasons other than symptoms of a hypersensitivity reaction, and if reinitiation of abacavir is under consideration, carefully evaluate the reason for discontinuation to ensure that the patient did not have symptoms of a hypersensitivity reaction. If the patient is of unknown HLA-B*5701 status, screening for the allele is recommended prior to reinitiation of TRIZIVIR.

If hypersensitivity cannot be ruled out, DO NOT reintroduce TRIZIVIR or any other abacavir-containing product. Even in the absence of the HLA-B*5701 allele, it is important to permanently discontinue abacavir and not rechallenge with abacavir if a hypersensitivity reaction cannot be ruled out on clinical grounds, due to the potential for a severe or even fatal reaction.

If symptoms consistent with hypersensitivity are not identified, reintroduction can be undertaken with continued monitoring for symptoms of a hypersensitivity reaction. Make patients aware that a hypersensitivity reaction can occur with reintroduction of abacavir and that abacavir reintroduction needs to be undertaken only if medical care can be readily accessed by the patient or others.

Risk Factor: HLA-B*5701 Allele: Trials have shown that carriage of the HLA-B*5701 allele is associated with a significantly increased risk of a hypersensitivity reaction to abacavir.

CNA106030 (PREDICT-1), a randomized, double-blind trial, evaluated the clinical utility of prospective HLA-B*5701 screening on the incidence of abacavir hypersensitivity reaction in abacavir-naive HIV-1-infected adults (n = 1,650). In this trial, use of pre-therapy screening for the HLA-B*5701 allele and exclusion of subjects with this allele reduced the incidence of clinically suspected abacavir hypersensitivity reactions from 7.8% (66/847) to 3.4% (27/803). Based on this trial, it is estimated that 61% of patients with the HLA-B*5701 allele will develop a clinically suspected hypersensitivity reaction during the course of abacavir treatment compared with 4% of patients who do not have the HLA-B*5701 allele.

Screening for carriage of the HLA-B*5701 allele is recommended prior to initiating treatment with abacavir. Screening is also recommended prior to reinitiation of abacavir in patients of unknown HLA-B*5701 status who have previously tolerated abacavir. For HLA-B*5701-positive patients, initiating or reinitiating treatment with an abacavir-containing regimen is not recommended and should be considered only with close medical supervision and under exceptional circumstances where potential benefit outweighs the risk.

Skin patch testing is used as a research tool and should not be used to aid in the clinical diagnosis of abacavir hypersensitivity.

In any patient treated with abacavir, the clinical diagnosis of hypersensitivity reaction must remain the basis of clinical decision-making. Even in the absence of the HLA-B*5701 allele, it is important to permanently discontinue abacavir and not rechallenge with abacavir if a hypersensitivity reaction cannot be ruled out on clinical grounds, due to the potential for a severe or even fatal reaction.

5.2 Hematologic Toxicity/Bone Marrow Suppression

Zidovudine, a component of TRIZIVIR, has been associated with hematologic toxicity including neutropenia and anemia, particularly in patients with advanced HIV-1 disease. TRIZIVIR should be used with caution in patients who have bone marrow compromise evidenced by granulocyte count less than 1,000 cells/mm^3 or hemoglobin less than 9.5 g/dL.

Frequent blood counts are strongly recommended in patients with advanced HIV-1 disease who are treated with TRIZIVIR. Periodic blood counts are recommended for other HIV-1-infected patients. If anemia or neutropenia develops, dosage interruption may be needed.

5.3 Myopathy

Myopathy and myositis, with pathological changes similar to that produced by HIV-1 disease, have been associated with prolonged use of zidovudine, and therefore may occur with therapy with TRIZIVIR.

5.4 Lactic Acidosis/Hepatomegaly With Steatosis

Lactic acidosis and severe hepatomegaly with steatosis, including fatal cases, have been reported with the use of nucleoside analogues alone or in combination, including abacavir, lamivudine, zidovudine, and other antiretrovirals. A majority of these cases have been in women. Obesity and prolonged nucleoside exposure may be risk factors. Particular caution should be exercised when administering TRIZIVIR to any patient with known risk factors for liver disease; however, cases have also been reported in patients with no known risk factors. Treatment with TRIZIVIR should be suspended in any patient who develops clinical or laboratory findings suggestive of lactic acidosis or pronounced hepatotoxicity (which may include hepatomegaly and steatosis even in the absence of marked transaminase elevations).

5.5 Patients With HIV-1 and Hepatitis B Virus Co-infection

Posttreatment Exacerbations of Hepatitis: In clinical trials in non-HIV-1-infected subjects treated with lamivudine for chronic HBV, clinical and laboratory evidence of exacerbations of hepatitis have occurred after discontinuation of lamivudine. These exacerbations have been detected primarily by serum ALT elevations in addition to re-emergence of hepatitis B viral DNA (HBV DNA). Although most events appear to have been self-limited, fatalities have been reported in some cases. Similar events have been reported from post-marketing experience after changes from lamivudine-containing HIV-1 treatment regimens to non-lamivudine-containing regimens in patients infected with both HIV-1 and HBV. The causal relationship to discontinuation of lamivudine treatment is unknown. Patients should be closely monitored with both clinical and laboratory follow-up for at least several months after stopping treatment. There is insufficient evidence to determine whether reinitiation of lamivudine alters the course of posttreatment exacerbations of hepatitis.

Emergence of Lamivudine-Resistant HBV: Safety and efficacy of lamivudine have not been established for treatment of chronic hepatitis B in subjects dually infected with HIV-1 and HBV. In non-HIV-infected subjects treated with lamivudine for chronic hepatitis B, emergence of lamivudine-resistant HBV has been detected and has been associated with diminished treatment response (see full prescribing information for EPIVIR-HBV® [lamivudine] for additional information). Emergence of hepatitis B virus variants associated with resistance to lamivudine has also been reported in HIV-1-infected subjects who have received lamivudine-containing antiretroviral regimens in the presence of concurrent infection with hepatitis B virus.

5.6 Use With Interferon- and Ribavirin-Based Regimens

In vitro studies have shown ribavirin can reduce the phosphorylation of pyrimidine nucleoside analogues such as lamivudine and zidovudine. Although no evidence of a pharmacokinetic or pharmacodynamic interaction (e.g., loss of HIV-1/HCV virologic suppression) was seen when ribavirin was coadministered with lamivudine or zidovudine in HIV-1/HCV co-infected subjects [see Clinical Pharmacology (12.3)], hepatic decompensation (some fatal) has occurred in HIV-1/HCV co-infected subjects receiving combination antiretroviral therapy for HIV-1 and interferon alfa with or without ribavirin. Patients receiving interferon alfa with or without ribavirin and TRIZIVIR should be closely monitored for treatment-associated toxicities, especially hepatic decompensation, neutropenia, and anemia. Discontinuation of TRIZIVIR should be considered as medically appropriate. Dose reduction or discontinuation of interferon alfa, ribavirin, or both should also be considered if worsening clinical toxicities are observed, including hepatic decompensation (e.g., Child-Pugh greater than 6) (see the complete prescribing information for interferon and ribavirin).

Exacerbation of anemia has been reported in HIV-1/HCV co-infected patients receiving ribavirin and zidovudine. Coadministration of ribavirin and TRIZIVIR is not advised.

5.7 Immune Reconstitution Syndrome

Immune reconstitution syndrome has been reported in patients treated with combination antiretroviral therapy, including TRIZIVIR. During the initial phase of combination antiretroviral treatment, patients whose immune systems respond may develop an inflammatory response to indolent or residual opportunistic infections (such as Mycobacterium avium infection, cytomegalovirus, Pneumocystis jirovecii pneumonia [PCP], or tuberculosis), which may necessitate further evaluation and treatment.

Autoimmune disorders (such as Graves’ disease, polymyositis, and Guillain-Barré syndrome) have also been reported to occur in the setting of immune reconstitution; however, the time to onset is more variable, and can occur many months after initiation of treatment.

5.8 Fat Redistribution

Redistribution/accumulation of body fat including central obesity, dorsocervical fat enlargement (buffalo hump), peripheral wasting, facial wasting, breast enlargement, and “cushingoid appearance” have been observed in patients receiving antiretroviral therapy. The mechanism and long-term consequences of these events are currently unknown. A causal relationship has not been established.

5.9 Myocardial Infarction

In a published prospective, observational, epidemiological trial designed to investigate the rate of myocardial infarction in patients on combination antiretroviral therapy, the use of abacavir within the previous 6 months was correlated with an increased risk of myocardial infarction (MI).^1 In a sponsor-conducted pooled analysis of clinical trials, no excess risk of myocardial infarction was observed in abacavir-treated subjects as compared with control subjects. In totality, the available data from the observational cohort and from clinical trials are inconclusive.

As a precaution, the underlying risk of coronary heart disease should be considered when prescribing antiretroviral therapies, including abacavir, and action taken to minimize all modifiable risk factors (e.g., hypertension, hyperlipidemia, diabetes mellitus, smoking).

5.10 Therapy Experienced Patients

In clinical trials, subjects with prolonged prior nucleoside reverse transcriptase inhibitor (NRTI) exposure or who had HIV-1 isolates that contained multiple mutations conferring resistance to NRTIs had limited response to abacavir. The potential for cross-resistance between abacavir and other NRTIs should be considered when choosing new therapeutic regimens in therapy-experienced patients [see Clinical Pharmacology (12.4)].

5.11 Use With Other Abacavir-, Lamivudine-, Zidovudine-, and/or Emtricitabine-Containing Products

TRIZIVIR is a fixed-dose combination of abacavir, lamivudine, and zidovudine and is intended only for patients whose regimen would otherwise include these 3 components. TRIZIVIR should not be administered concomitantly with other abacavir-, lamivudine-, or zidovudine-containing products including ZIAGEN (abacavir sulfate) Tablets and Oral Solution, EPIVIR® (lamivudine) Tablets and Oral Solution, EPIVIR-HBV (lamivudine) Tablets and Oral Solution, RETROVIR® (zidovudine) Tablets, Capsules, Syrup, and IV Infusion, COMBIVIR® (lamivudine and zidovudine) Tablets, EPZICOM® (abacavir sulfate and lamivudine) Tablets; or emtricitabine‑containing products, including ATRIPLA® (efavirenz/emtricitabine/tenofovir disoproxil fumarate) Tablets, EMTRIVA® (emtricitabine) Capsules and Oral Solution, TRUVADA® (emtricitabine/tenofovir disoproxil fumarate) Tablets, or COMPLERA® (emtricitabine/rilpirivine/tenofovir disoproxil fumarate) Tablets.

The complete prescribing information for all agents being considered for use with TRIZIVIR should be consulted before combination therapy with TRIZIVIR is initiated.

6 ADVERSE REACTIONS

The following adverse reactions are discussed in greater detail in other sections of the labeling:

- Serious and sometimes fatal hypersensitivity reactions [see Boxed Warning, Warnings and Precautions (5.1)].
- Hematologic toxicity, including neutropenia and anemia [see Boxed Warning, Warnings and Precautions (5.2)].
- Symptomatic myopathy [see Boxed Warning, Warnings and Precautions (5.3)].
- Lactic acidosis and severe hepatomegaly with steatosis [see Boxed Warning, Warnings and Precautions (5.4)].
- Acute exacerbations of hepatitis B [see Boxed Warning, Warnings and Precautions (5.5)].
- Hepatic decompensation in patients co-infected with HIV-1 and hepatitis C [see Warnings and Precautions (5.6)].
- Exacerbation of anemia in HIV-1/HCV co-infected patients receiving ribavirin and zidovudine [see Warnings and Precautions (5.6)].
- Immune reconstitution syndrome [see Warnings and Precautions (5.7)].
- Fat redistribution [see Warnings and Precautions (5.8)].
- Myocardial infarction [see Warnings and Precautions (5.9)].

6.1 Clinical Trials Experience

Because clinical trials are conducted under widely varying conditions, adverse reaction rates observed in the clinical trials of a drug cannot be directly compared with rates in the clinical trials of another drug and may not reflect the rates observed in clinical practice.

Treatment-emergent clinical adverse reactions (rated by the investigator as moderate or severe) with a frequency greater than or equal to 5% during therapy with abacavir 300 mg twice daily, lamivudine 150 mg twice daily, and zidovudine 300 mg twice daily compared with indinavir 800 mg 3 times daily, lamivudine 150 mg twice daily, and zidovudine 300 mg twice daily from CNA3005 are listed in Table 1.

Table 1. Treatment-Emergent (All Causality) Adverse Reactions of at Least Moderate Intensity (Grades 2-4, ≥5% Frequency) in Therapy-Naive Adults (CNA3005) Through 48 Weeks of Treatment
Adverse Reaction | ZIAGEN plus; Lamivudine/Zidovudine; (n = 262) | Indinavir plus; Lamivudine/Zidovudine; (n = 264)
Nausea | 19% | 17%
Headache | 13% | 9%
Malaise and fatigue | 12% | 12%
Nausea and vomiting | 10% | 10%
Hypersensitivity reaction | 8% | 2%
Diarrhea | 7% | 5%
Fever and/or chills | 6% | 3%
Depressive disorders | 6% | 4%
Musculoskeletal pain | 5% | 7%
Skin rashes | 5% | 4%
Ear/nose/throat infections | 5% | 4%
Viral respiratory infections | 5% | 5%
Anxiety | 5% | 3%
Renal signs/symptoms | <1% | 5%
Pain (non-site-specific) | <1% | 5%

Five subjects receiving abacavir in CNA3005 experienced worsening of pre-existing depression compared to none in the indinavir arm. The background rates of pre-existing depression were similar in the 2 treatment arms.

Laboratory Abnormalities: Laboratory abnormalities in CNA3005 are listed in Table 2.

Table 2. Treatment-Emergent Laboratory Abnormalities (Grades 3/4) in CNA3005
Grade 3/4 Laboratory Abnormalities | Number of Subjects by Treatment Group
Grade 3/4 Laboratory Abnormalities | ZIAGEN plus; Lamivudine/Zidovudine; (n = 262) | Indinavir plus; Lamivudine/Zidovudine; (n = 264)
Elevated CPK (>4 x ULN) | 18 (7%) | 18 (7%)
ALT (>5.0 x ULN) | 16 (6%) | 16 (6%)
Neutropenia (<750/mm^3) | 13 (5%) | 13 (5%)
Hypertriglyceridemia (>750 mg/dL) | 5 (2%) | 3 (1%)
Hyperamylasemia (>2.0 x ULN) | 5 (2%) | 1 (<1%)
Hyperglycemia (>13.9 mmol/L) | 2 (<1%) | 2 (<1%)
Anemia (Hgb ≤6.9 g/dL) | 0 (0%) | 3 (1%)
ULN = Upper limit of normal.
n = Number of patients assessed.

Other Adverse Events: In addition to adverse reactions in Tables 1 and 2, other adverse events observed in the expanded access program for abacavir were pancreatitis and increased GGT.

6.2 Postmarketing Experience

In addition to adverse reactions reported from clinical trials, the following reactions have been identified during postmarketing use of abacavir, lamivudine, and/or zidovudine. Because they are reported voluntarily from a population of unknown size, estimates of frequency cannot be made. These reactions have been chosen for inclusion due to a combination of their seriousness, frequency of reporting, or potential causal connection to abacavir, lamivudine and/or zidovudine.

Abacavir:

Cardiovascular: Myocardial infarction.

Skin: Suspected Stevens-Johnson syndrome (SJS) and toxic epidermal necrolysis (TEN) have been reported in patients receiving abacavir primarily in combination with medications known to be associated with SJS and TEN, respectively. Because of the overlap of clinical signs and symptoms between hypersensitivity to abacavir and SJS and TEN, and the possibility of multiple drug sensitivities in some patients, abacavir should be discontinued and not restarted in such cases.

There have also been reports of erythema multiforme with abacavir use.

Abacavir, Lamivudine, and/or Zidovudine:

Body as a Whole: Redistribution/accumulation of body fat [see Warnings and Precautions (5.8)].

Cardiovascular: Cardiomyopathy.

Digestive: Stomatitis.

Endocrine and Metabolic: Gynecomastia, hyperglycemia.

Gastrointestinal: Anorexia and/or decreased appetite, abdominal pain, dyspepsia, oral mucosal pigmentation.

General: Vasculitis, weakness.

Hemic and Lymphatic: Aplastic anemia, anemia (including pure red cell aplasia and severe anemias progressing on therapy), lymphadenopathy, splenomegaly, thrombocytopenia.

Hepatic: Lactic acidosis and hepatic steatosis [see Warnings and Precautions (5.4)], elevated bilirubin, elevated transaminases, posttreatment exacerbation of hepatitis B [see Warnings and Precautions (5.5)].

Hypersensitivity: Sensitization reactions (including anaphylaxis), urticaria.

Musculoskeletal: Arthralgia, myalgia, muscle weakness, CPK elevation, rhabdomyolysis.

Nervous: Dizziness, paresthesia, peripheral neuropathy, seizures.

Psychiatric: Insomnia and other sleep disorders.

Respiratory: Abnormal breath sounds/wheezing.

Skin: Alopecia, erythema multiforme, Stevens-Johnson syndrome.

7 DRUG INTERACTIONS

- No drug interaction trials have been conducted using TRIZIVIR Tablets [see Clinical Pharmacology (12.3)].

7.1 Antiretroviral Agents

Zidovudine: Stavudine: Concomitant use of zidovudine with stavudine should be avoided since an antagonistic relationship has been demonstrated in vitro.

Nucleoside Analogues Affecting DNA Replication: Some nucleoside analogues affecting DNA replication, such as ribavirin, antagonize the in vitro antiviral activity of zidovudine against HIV-1; concomitant use of such drugs should be avoided.

7.2 Doxorubicin

Zidovudine: Concomitant use of zidovudine with doxorubicin should be avoided since an antagonistic relationship has been demonstrated in vitro.

7.3 Ethanol

Abacavir: Abacavir has no effect on the pharmacokinetic properties of ethanol. Ethanol decreases the elimination of abacavir causing an increase in overall exposure [see Clinical Pharmacology (12.3)].

7.4 Hematologic/Bone Marrow Suppressive/Cytotoxic Agents

Zidovudine: Coadministration of ganciclovir, interferon alfa, ribavirin, and other bone marrow suppressive or cytotoxic agents may increase the hematologic toxicity of zidovudine.

7.5 Interferon- and Ribavirin-Based Regimens

Lamivudine: Although no evidence of a pharmacokinetic or pharmacodynamic interaction (e.g., loss of HIV-1/HCV virologic suppression) was seen when ribavirin was coadministered with lamivudine in HIV-1/HCV co-infected subjects, hepatic decompensation (some fatal) has occurred in HIV-1/HCV co-infected subjects receiving combination antiretroviral therapy for HIV-1 and interferon alfa with or without ribavirin [see Warnings and Precautions (5.6), Clinical Pharmacology (12.3)].

7.6 Methadone

Abacavir: The addition of methadone has no clinically significant effect on the pharmacokinetic properties of abacavir. In a trial of 11 HIV-1-infected subjects receiving methadone-maintenance therapy with 600 mg of ZIAGEN twice daily (twice the currently recommended dose), oral methadone clearance increased [see Clinical Pharmacology (12.3)]. This alteration will not result in a methadone dose modification in the majority of patients; however, an increased methadone dose may be required in a small number of patients.

7.7 Trimethoprim/Sulfamethoxazole (TMP/SMX)

Lamivudine: No change in dose of either drug is recommended [see Clinical Pharmacology (12.3)]. There is no information regarding the effect on lamivudine pharmacokinetics of higher doses of TMP/SMX such as those used to treat PCP.

8 USE IN SPECIFIC POPULATIONS

8.1 Pregnancy

TRIZIVIR: Pregnancy Category C. There are no adequate and well-controlled studies of TRIZIVIR in pregnant women. Reproduction studies with abacavir, lamivudine, and zidovudine have been performed in animals (see Abacavir, Lamivudine, and Zidovudine sections below). TRIZIVIR should be used during pregnancy only if the potential benefits outweigh the risks.

Abacavir: Studies in pregnant rats showed that abacavir is transferred to the fetus through the placenta. Fetal malformations (increased incidences of fetal anasarca and skeletal malformations) and developmental toxicity (depressed fetal body weight and reduced crown-rump length) were observed in rats at a dose which produced 35 times the human exposure, based on AUC. Embryonic and fetal toxicities (increased resorptions, decreased fetal body weights) and toxicities to the offspring (increased incidence of stillbirth and lower body weights) occurred at half of the above-mentioned dose in separate fertility studies conducted in rats. In the rabbit, no developmental toxicity and no increases in fetal malformations occurred at doses that produced 8.5 times the human exposure at the recommended dose based on AUC.

Lamivudine: Studies in pregnant rats showed that lamivudine is transferred to the fetus through the placenta. Reproduction studies with orally administered lamivudine have been performed in rats and rabbits at doses producing plasma levels up to approximately 35 times that for the recommended adult HIV dose. No evidence of teratogenicity due to lamivudine was observed. Evidence of early embryolethality was seen in the rabbit at exposure levels similar to those observed in humans, but there was no indication of this effect in the rat at exposure levels up to 35 times those in humans.

Zidovudine: Reproduction studies with orally administered zidovudine in the rat and in the rabbit at doses up to 500 mg/kg/day revealed no evidence of teratogenicity with zidovudine. Zidovudine treatment resulted in embryo/fetal toxicity as evidenced by an increase in the incidence of fetal resorptions in rats given 150 or 450 mg/kg/day and rabbits given 500 mg/kg/day. The doses used in the teratology studies resulted in peak zidovudine plasma concentrations (after one half of the daily dose) in rats 66 to 226 times, and in rabbits 12 to 87 times, mean steady-state peak human plasma concentrations (after one sixth of the daily dose) achieved with the recommended daily dose (100 mg every 4 hours). In an additional teratology study in rats, a dose of 3,000 mg/kg/day (very near the oral median lethal dose in rats of approximately 3,700 mg/kg) caused marked maternal toxicity and an increase in the incidence of fetal malformations. This dose resulted in peak zidovudine plasma concentrations 350 times peak human plasma concentrations. No evidence of teratogenicity was seen in this experiment at doses of 600 mg/kg/day or less. Two rodent carcinogenicity studies were conducted [see Nonclinical Toxicology (13.1)].

Antiretroviral Pregnancy Registry: To monitor maternal-fetal outcomes of pregnant women exposed to TRIZIVIR or other antiretroviral agents, an Antiretroviral Pregnancy Registry has been established. Physicians are encouraged to register patients by calling 1-800-258-4263.

8.3 Nursing Mothers

The Centers for Disease Control and Prevention recommend that HIV-1-infected mothers not breastfeed their infants to avoid risking postnatal transmission of HIV infection.

Abacavir, Lamivudine, and Zidovudine: Lamivudine and zidovudine are excreted in human breast milk; abacavir and lamivudine are secreted into the milk of lactating rats.

Because of both the potential for HIV-1 transmission and the potential for serious adverse reactions in nursing infants, mothers should be instructed not to breastfeed if they are receiving TRIZIVIR.

8.4 Pediatric Use

TRIZIVIR is not intended for use in pediatric patients and is not recommended in adolescents who weigh less than 40 kg because it is a fixed-dose tablet that cannot be adjusted for these patient populations.

Therapy-Experienced Pediatric Trial: A randomized, double-blind trial, CNA3006, compared ZIAGEN plus lamivudine and zidovudine versus lamivudine and zidovudine in pediatric subjects, most of whom were extensively pretreated with nucleoside analogue antiretroviral agents. Subjects in this trial had a limited response to abacavir.

8.5 Geriatric Use

Clinical studies of abacavir, lamivudine, and zidovudine did not include sufficient numbers of subjects aged 65 and over to determine whether they respond differently from younger subjects. In general, dose selection for an elderly patient should be cautious, reflecting the greater frequency of decreased hepatic, renal, or cardiac function, and of concomitant disease or other drug therapy [see Dosage and Administration (2.3), Use in Specific Populations (8.6)].

8.6 Patients With Impaired Renal Function

TRIZIVIR is not recommended for patients with impaired renal function (i.e., creatinine clearance <50 mL/min) because TRIZIVIR is a fixed-dose combination and the dosage of the individual components cannot be adjusted.

8.7 Patients With Impaired Hepatic Function

TRIZIVIR is contraindicated for patients with hepatic impairment because TRIZIVIR is a fixed-dose combination and the dosage of the individual components cannot be adjusted.

10 OVERDOSAGE

Abacavir: There is no known antidote for abacavir. It is not known whether abacavir can be removed by peritoneal dialysis or hemodialysis.

Lamivudine: One case of an adult ingesting 6 grams of lamivudine was reported; there were no clinical signs or symptoms noted and hematologic tests remained normal. It is not known whether lamivudine can be removed by peritoneal dialysis or hemodialysis.

Zidovudine: Acute overdoses of zidovudine have been reported in pediatric patients and adults. These involved exposures up to 50 grams. The only consistent findings were nausea and vomiting. Other reported occurrences included headache, dizziness, drowsiness, lethargy, and confusion. Hematologic changes were transient. All patients recovered. Hemodialysis and peritoneal dialysis appear to have a negligible effect on the removal of zidovudine, while elimination of its primary metabolite, 3′-azido-3′-deoxy-5′-O-β-D-glucopyranuronosylthymidine (GZDV), is enhanced.

11 DESCRIPTION

TRIZIVIR: TRIZIVIR Tablets contain the following 3 synthetic nucleoside analogues: abacavir sulfate (ZIAGEN), lamivudine (also known as EPIVIR or 3TC), and zidovudine (also known as RETROVIR, azidothymidine, or ZDV) with inhibitory activity against HIV-1.

TRIZIVIR Tablets are for oral administration. Each film-coated tablet contains the active ingredients 300 mg of abacavir as abacavir sulfate, 150 mg of lamivudine, and 300 mg of zidovudine, and the inactive ingredients magnesium stearate, microcrystalline cellulose, and sodium starch glycolate. The tablets are coated with a film (OPADRY® green 03B11434) that is made of FD&C Blue No. 2, hypromellose, polyethylene glycol, titanium dioxide, and yellow iron oxide.

Abacavir Sulfate: The chemical name of abacavir sulfate is (1S,cis)-4-[2-amino-6-(cyclopropylamino)-9H-purin-9-yl]-2-cyclopentene-1-methanol sulfate (salt) (2:1). Abacavir sulfate is the enantiomer with 1S, 4R absolute configuration on the cyclopentene ring. It has a molecular formula of (C14H18N6O)2•H2SO4 and a molecular weight of 670.76 daltons. It has the following structural formula:

Abacavir sulfate is a white to off-white solid with a solubility of approximately 77 mg/mL in distilled water at 25°C.

In vivo, abacavir sulfate dissociates to its free base, abacavir. In this insert, all dosages for ZIAGEN (abacavir sulfate) are expressed in terms of abacavir.

Lamivudine: The chemical name of lamivudine is (2R,cis)-4-amino-1-(2-hydroxymethyl-1,3-oxathiolan-5-yl)-(1H)-pyrimidin-2-one. Lamivudine is the (-)enantiomer of a dideoxy analogue of cytidine. Lamivudine has also been referred to as (-)2′,3′-dideoxy, 3′-thiacytidine. It has a molecular formula of C8H11N3O3S and a molecular weight of 229.3 daltons. It has the following structural formula:

Lamivudine is a white to off-white crystalline solid with a solubility of approximately 70 mg/mL in water at 20°C.

Zidovudine: The chemical name of zidovudine is 3′-azido-3′-deoxythymidine. It has a molecular formula of C10H13N5O4 and a molecular weight of 267.24 daltons. It has the following structural formula:

Zidovudine is a white to beige, crystalline solid with a solubility of 20.1 mg/mL in water at 25°C.

12 CLINICAL PHARMACOLOGY

12.1 Mechanism of Action

TRIZIVIR is an antiviral agent [see Clinical Pharmacology (12.4)].

12.3 Pharmacokinetics

Pharmacokinetics in Adults: TRIZIVIR: In a single-dose, 3-way crossover bioavailability trial of 1 TRIZIVIR Tablet versus 1 ZIAGEN Tablet (300 mg), 1 EPIVIR Tablet (150 mg), plus 1 RETROVIR Tablet (300 mg) administered simultaneously in healthy subjects (n = 24), there was no difference in the extent of absorption, as measured by the area under the plasma concentration-time curve (AUC) and maximal peak concentration (Cmax), of all 3 components. One TRIZIVIR Tablet was bioequivalent to 1 ZIAGEN Tablet (300 mg), 1 EPIVIR Tablet (150 mg), plus 1 RETROVIR Tablet (300 mg) following single-dose administration to fasting healthy subjects (n = 24).

Abacavir: Following oral administration, abacavir is rapidly absorbed and extensively distributed. Binding of abacavir to human plasma proteins is approximately 50%. Binding of abacavir to plasma proteins was independent of concentration. Total blood and plasma drug-related radioactivity concentrations are identical, demonstrating that abacavir readily distributes into erythrocytes. The primary routes of elimination of abacavir are metabolism by alcohol dehydrogenase to form the 5′-carboxylic acid and glucuronyl transferase to form the 5′-glucuronide.

Lamivudine: Following oral administration, lamivudine is rapidly absorbed and extensively distributed. Binding to plasma protein is low. Approximately 70% of an intravenous dose of lamivudine is recovered as unchanged drug in the urine. Metabolism of lamivudine is a minor route of elimination. In humans, the only known metabolite is the trans-sulfoxide metabolite (approximately 5% of an oral dose after 12 hours).

Zidovudine: Following oral administration, zidovudine is rapidly absorbed and extensively distributed. Binding to plasma protein is low. Zidovudine is eliminated primarily by hepatic metabolism. The major metabolite of zidovudine is GZDV. GZDV AUC is about 3-fold greater than the zidovudine AUC. Urinary recovery of zidovudine and GZDV accounts for 14% and 74% of the dose following oral administration, respectively. A second metabolite, 3′-amino-3′-deoxythymidine (AMT), has been identified in plasma. The AMT AUC was one-fifth of the zidovudine AUC.

In humans, abacavir, lamivudine, and zidovudine are not significantly metabolized by cytochrome P450 enzymes.

The pharmacokinetic properties of abacavir, lamivudine, and zidovudine in fasting subjects are summarized in Table 3.

Table 3. Pharmacokinetic Parametersa for Abacavir, Lamivudine, and Zidovudine in Adults
Parameter | Abacavir |  | Lamivudine |  | Zidovudine
Oral bioavailability (%) | 86 ± 25 | n = 6 | 86 ± 16 | n = 12 | 64 ± 10 | n = 5
Apparent volume of distribution (L/kg) | 0.86 ± 0.15 | n = 6 | 1.3 ± 0.4 | n = 20 | 1.6 ± 0.6 | n = 8
Systemic clearance (L/h/kg) | 0.80 ± 0.24 | n = 6 | 0.33 ± 0.06 | n = 20 | 1.6 ± 0.6 | n = 6
Renal clearance (L/h/kg) | .007 ± .008 | n = 6 | 0.22 ± 0.06 | n = 20 | 0.34 ± 0.05 | n = 9
Elimination half-life (h) | 1.45 ± 0.32 | n = 20 | 5 to 7b |  | 0.5 to 3b
a Data presented as mean ± standard deviation except where noted.
b Approximate range.

Effect of Food on Absorption of TRIZIVIR: Administration with food in a single-dose bioavailability trial resulted in lower Cmax, similar to results observed previously for the reference formulations. The average [90% CI] decrease in abacavir, lamivudine, and zidovudine Cmax was 32% [24% to 38%], 18% [10% to 25%], and 28% [13% to 40%], respectively, when administered with a high-fat meal, compared with administration under fasted conditions. Administration of TRIZIVIR with food did not alter the extent of abacavir, lamivudine, and zidovudine absorption (AUC), as compared with administration under fasted conditions (n = 24) [see Dosage and Administration (2.1)].

Special Populations: Renal Impairment: TRIZIVIR: Because lamivudine and zidovudine require dose adjustment in the presence of renal insufficiency, TRIZIVIR is not recommended for use in patients with creatinine clearance <50 mL/min [see Use in Specific Populations (8.6)].

Hepatic Impairment: TRIZIVIR: TRIZIVIR is contraindicated for patients with impaired hepatic function because TRIZIVIR is a fixed-dose combination and the dosage of the individual components cannot be adjusted. Abacavir is contraindicated in patients with moderate to severe hepatic impairment and dose reduction is required in patients with mild hepatic impairment.

Pregnancy: See Use in Specific Populations (8.1).

Abacavir and Lamivudine: No data are available on the pharmacokinetics of abacavir or lamivudine during pregnancy.

Zidovudine: Zidovudine pharmacokinetics have been studied in a Phase 1 trial of 8 women during the last trimester of pregnancy. As pregnancy progressed, there was no evidence of drug accumulation. The pharmacokinetics of zidovudine were similar to that of nonpregnant adults. Consistent with passive transmission of the drug across the placenta, zidovudine concentrations in neonatal plasma at birth were essentially equal to those in maternal plasma at delivery. Although data are limited, methadone maintenance therapy in 5 pregnant women did not appear to alter zidovudine pharmacokinetics. In a nonpregnant adult population, a potential for interaction has been identified [see Use in Specific Populations (8.1)].

Nursing Mothers: See Use in Specific Populations (8.3).

Abacavir: No data are available on the pharmacokinetics of abacavir in nursing mothers.

Lamivudine: Samples of breast milk obtained from 20 mothers receiving lamivudine monotherapy (300 mg twice daily) or combination therapy (150 mg lamivudine twice daily and 300 mg zidovudine twice daily) had measurable concentrations of lamivudine.

Zidovudine: After administration of a single dose of 200 mg zidovudine to 13 HIV‑1-infected women, the mean concentration of zidovudine was similar in human milk and serum [see Use in Specific Populations (8.3)].

Pediatric Patients: TRIZIVIR is not intended for use in pediatric patients. TRIZIVIR is not recommended in adolescents who weigh less than 40 kg because it is a fixed-dose tablet that cannot be dose adjusted for this patient population.

Geriatric Patients: The pharmacokinetics of abacavir, lamivudine, and zidovudine have not been studied in subjects over 65 years of age.

Gender:

Abacavir: A population pharmacokinetic analysis in HIV-1-infected male (n = 304) and female (n = 67) subjects showed no gender differences in abacavir AUC normalized for lean body weight.

Lamivudine and Zidovudine: A pharmacokinetic trial in healthy male (n = 12) and female (n = 12) subjects showed no gender differences in zidovudine exposure (AUC∞) or lamivudine (AUC∞) normalized for body weight.

Race:

Abacavir: There are no significant differences between blacks and Caucasians in abacavir pharmacokinetics.

Lamivudine: There are no significant racial differences in lamivudine pharmacokinetics.

Zidovudine: The pharmacokinetics of zidovudine with respect to race have not been determined.

Drug Interactions: The drug interactions described below are based on trials conducted with the individual nucleoside analogues.

Cytochrome P450: In humans, abacavir, lamivudine, and zidovudine are not significantly metabolized by cytochrome P450 enzymes; therefore, it is unlikely that clinically significant drug interactions will occur with drugs metabolized through these pathways.

Glucuronyl Transferase: Due to the common metabolic pathways of abacavir and zidovudine via glucuronyl transferase, 15 HIV-1-infected subjects were enrolled in a crossover trial evaluating single doses of abacavir (600 mg), lamivudine (150 mg), and zidovudine (300 mg) alone or in combination. Analysis showed no clinically relevant changes in the pharmacokinetics of abacavir with the addition of lamivudine or zidovudine or the combination of lamivudine and zidovudine. Lamivudine exposure (AUC decreased 15%) and zidovudine exposure (AUC increased 10%) did not show clinically relevant changes with concurrent abacavir.

Lamivudine and Zidovudine: No clinically significant alterations in lamivudine or zidovudine pharmacokinetics were observed in 12 asymptomatic HIV-1-infected adult subjects given a single dose of zidovudine (200 mg) in combination with multiple doses of lamivudine (300 mg q 12 h).

Methadone: In a trial of 11 HIV-1-infected subjects receiving methadone-maintenance therapy (40 mg and 90 mg daily), with 600 mg of ZIAGEN twice daily (twice the currently recommended dose), oral methadone clearance increased 22% (90% CI: 6% to 42%) [see Drug Interactions (7.6)].

Ribavirin: In vitro data indicate ribavirin reduces phosphorylation of lamivudine, stavudine, and zidovudine. However, no pharmacokinetic (e.g., plasma concentrations or intracellular triphosphorylated active metabolite concentrations) or pharmacodynamic (e.g., loss of HIV-1/HCV virologic suppression) interaction was observed when ribavirin and lamivudine (n = 18), stavudine (n = 10), or zidovudine (n = 6) were coadministered as part of a multi-drug regimen to HIV-1/HCV co-infected subjects [see Warnings and Precautions (5.6)].

The effects of other coadministered drugs on abacavir, lamivudine, or zidovudine are provided in Table 4.

Table 4. Effect of Coadministered Drugs on Abacavir, Lamivudine, and Zidovudine AUCa Note: ROUTINE DOSE MODIFICATION OF ABACAVIR, LAMIVUDINE, AND ZIDOVUDINE IS NOT WARRANTED WITH COADMINISTRATION OF THE FOLLOWING DRUGS.
Drugs That May Alter Lamivudine Blood Concentrations
Coadministered Drug and Dose | Lamivudine Dose | n | Lamivudine Concentrations |  | Concentration of Coadministered Drug
Coadministered Drug and Dose | Lamivudine Dose | n | AUC | Variability | Concentration of Coadministered Drug
Nelfinavir; 750 mg q 8 h; x 7 to 10 days | single 150 mg | 11 | ↑10% | 95% CI:; 1% to 20% | ↔
Trimethoprim 160 mg/; Sulfamethoxazole; 800 mg daily; x 5 days | single 300 mg | 14 | ↑43% | 90% CI:; 32% to 55% | ↔
Drugs That May Alter Zidovudine Blood Concentrations
Coadministered Drug and Dose | Zidovudine Dose | n | Zidovudine Concentrations |  | Concentration of Coadministered Drug
Coadministered Drug and Dose | Zidovudine Dose | n | AUC | Variability | Concentration of Coadministered Drug
Atovaquone; 750 mg q 12 h; with food | 200 mg q 8 h | 14 | ↑31% | Range; 23% to 78%b | ↔
Clarithromycin; 500 mg twice daily | 100 mg q 4 h x 7 days | 4 | ↓12% | Range ↓34% to ↑14% | Not Reported
Fluconazole; 400 mg daily | 200 mg q 8 h | 12 | ↑74% | 95% CI:; 54% to 98% | Not Reported
Methadone; 30 to 90 mg daily | 200 mg q 4 h | 9 | ↑43% | Range; 16% to 64%b | ↔
Nelfinavir; 750 mg q 8 h x 7 to; 10 days | single 200 mg | 11 | ↓35% | Range; 28% to 41% | ↔
Probenecid; 500 mg q 6 h x; 2 days | 2 mg/kg q 8 h x 3 days | 3 | ↑106% | Range; 100% to 170%b | Not Assessed
Rifampin; 600 mg daily x 14 days | 200 mg q 8 h x 14 days | 8 | ↓47% | 90% CI: 41% to 53% | Not Assessed
Ritonavir; 300 mg q 6 h x; 4 days | 200 mg q 8 h x 4 days | 9 | ↓25% | 95% CI:; 15% to 34% | ↔
Valproic acid; 250 mg or 500 mg; q 8 h x 4 days | 100 mg q 8 h x 4 days | 6 | ↑80% | Range; 64% to 130%b | Not Assessed
Drugs That May Alter Abacavir Blood Concentrations
Coadministered Drug and Dose | Abacavir Dose | n | Abacavir Concentrations |  | Concentration of Coadministered Drug
Coadministered Drug and Dose | Abacavir Dose | n | AUC | Variability | Concentration of Coadministered Drug
Ethanol; 0.7 g/kg | single 600 mg | 24 | ↑41% | 90% CI:; 35% to 48% | ↔
↑ = Increase; ↓ = Decrease; ↔ = no significant change; AUC = area under the concentration versus time curve; CI = confidence interval.
a See Drug Interactions (7) for additional information on drug interactions.
b Estimated range of percent difference.

12.4 Microbiology

Mechanism of Action: Abacavir: Abacavir is a carbocyclic synthetic nucleoside analogue. Abacavir is converted by cellular enzymes to the active metabolite, carbovir triphosphate (CBV-TP), an analogue of deoxyguanosine-5′-triphosphate (dGTP). CBV-TP inhibits the activity of HIV-1 reverse transcriptase (RT) both by competing with the natural substrate dGTP and by its incorporation into viral DNA. The lack of a 3′-OH group in the incorporated nucleotide analogue prevents the formation of the 5′ to 3′ phosphodiester linkage essential for DNA chain elongation, and therefore, the viral DNA growth is terminated. CBV-TP is a weak inhibitor of cellular DNA polymerases α, β, and γ.

Lamivudine: Lamivudine is a synthetic nucleoside analogue. Intracellularly, lamivudine is phosphorylated to its active 5′-triphosphate metabolite, lamivudine triphosphate (3TC-TP). The principal mode of action of 3TC-TP is inhibition of RT via DNA chain termination after incorporation of the nucleotide analogue. 3TC-TP is a weak inhibitor of cellular DNA polymerases α, β, and γ.

Zidovudine: Zidovudine is a synthetic nucleoside analogue. Intracellularly, zidovudine is phosphorylated to its active 5′-triphosphate metabolite, zidovudine triphosphate (ZDV-TP). The principal mode of action of ZDV-TP is inhibition of RT via DNA chain termination after incorporation of the nucleotide analogue. ZDV-TP is a weak inhibitor of the cellular DNA polymerases α and γ and has been reported to be incorporated into the DNA of cells in culture.

Antiviral Activity: Abacavir: The antiviral activity of abacavir against HIV-1 was evaluated against a T-cell tropic laboratory strain HIV-1IIIB in lymphoblastic cell lines, a monocyte/macrophage tropic laboratory strain HIV-1BaL in primary monocytes/macrophages, and clinical isolates in peripheral blood mononuclear cells. The concentration of drug necessary to effect viral replication by 50 percent (EC50) ranged from 3.7 to 5.8 μM (1 μM = 0.28 mcg/mL) and 0.07 to 1.0 μM against HIV-1IIIB and HIV-1BaL, respectively, and was 0.26 ± 0.18 μM against 8 clinical isolates. The EC50 values of abacavir against different HIV-1 clades (A-G) ranged from 0.0015 to 1.05 μM, and against HIV-2 isolates, from 0.024 to 0.49 μM. Abacavir had synergistic activity in cell culture in combination with the NRTI zidovudine, the non-nucleoside reverse transcriptase inhibitor (NNRTI) nevirapine, and the protease inhibitor (PI) amprenavir; and additive activity in combination with the NRTIs didanosine, emtricitabine, lamivudine, stavudine, tenofovir, and zalcitabine. Ribavirin (50 μM) had no effect on the anti–HIV-1 activity of abacavir in cell culture.

Lamivudine: The antiviral activity of lamivudine against HIV-1 was assessed in a number of cell lines (including monocytes and fresh human peripheral blood lymphocytes) using standard susceptibility assays. EC50 values (50% effective concentrations) were in the range of 0.003 to 15 μM (1 μM = 0.23 mcg/mL). HIV-1 from therapy-naive subjects with no amino acid substitutions associated with resistance gave median EC50 values of 0.429 µM (range: 0.200 to 2.007 µM) from Virco (n = 92 baseline samples from COLA40263) and 2.35 µM (1.37 to 3.68 µM) from Monogram Biosciences (n = 135 baseline samples from ESS30009). The EC50 values of lamivudine against different HIV-1 clades (A-G) ranged from 0.001 to 0.120 µM, and against HIV-2 isolates from 0.003 to 0.120 μM in peripheral blood mononuclear cells. Ribavirin (50 μM) decreased the anti-HIV-1 activity of lamivudine by 3.5-fold in MT-4 cells.

Zidovudine: The antiviral activity of zidovudine against HIV-1 was assessed in a number of cell lines (including monocytes and fresh human peripheral blood lymphocytes). The EC50 and EC90 values for zidovudine were 0.01 to 0.49 µM (1 μM = 0.27 mcg/mL) and 0.1 to 9 μM, respectively. HIV-1 from therapy-naive subjects with no amino acid substitutions associated with resistance gave median EC50 values of 0.011 µM (range: 0.005 to 0.110 µM) from Virco (n = 92 baseline samples from COLA40263) and 0.0017 µM (0.006 to 0.0340 µM) from Monogram Biosciences (n = 135 baseline samples from ESS30009). The EC50 values of zidovudine against different HIV-1 clades (A-G) ranged from 0.00018 to 0.02 μM, and against HIV-2 isolates from 0.00049 to 0.004 μM. In cell culture drug combination studies, zidovudine demonstrates synergistic activity with the NRTIs abacavir, didanosine, lamivudine, and zalcitabine; the NNRTIs delavirdine and nevirapine; and the PIs indinavir, nelfinavir, ritonavir, and saquinavir; and additive activity with interferon alfa. Ribavirin has been found to inhibit the phosphorylation of zidovudine in cell culture.

Resistance: HIV-1 isolates with reduced sensitivity to abacavir, lamivudine, or zidovudine have been selected in cell culture and were also obtained from subjects treated with abacavir, lamivudine, and zidovudine, or the combination of lamivudine and zidovudine.

Abacavir: Genotypic analysis of isolates selected in cell culture and recovered from abacavir-treated subjects demonstrated that amino acid substitutions K65R, L74V, Y115F, and M184V/I in HIV-1 RT contributed to abacavir resistance. In a trial of subjects receiving abacavir once or twice daily in combination with lamivudine and efavirenz once daily, 39% (7/18) of the isolates from subjects who experienced virologic failure in the abacavir once-daily arm had a >2.5-fold decrease in abacavir susceptibility with a median-fold decrease of 1.3 (range: 0.5 to 11) compared with 29% (5/17) of the failure isolates in the twice-daily arm with a median-fold decrease of 0.92 (range: 0.7 to 13).

Lamivudine: Genotypic analysis of isolates selected in cell culture and recovered from lamivudine-treated subjects showed that the resistance was due to a specific amino acid substitution in the HIV-1 RT at codon 184 changing the methionine to either valine or isoleucine (M184V/I).

Zidovudine: Genotypic analyses of the isolates selected in cell culture and recovered from zidovudine-treated subjects showed mutations in the HIV-1 RT gene resulting in 6 amino acid substitutions (M41L, D67N, K70R, L210W, T215Y or F, and K219Q) that confer zidovudine resistance. In general, higher levels of resistance were associated with greater number of mutations. In some subjects harboring zidovudine-resistant virus at baseline, phenotypic sensitivity to zidovudine was restored by 12 weeks of treatment with lamivudine and zidovudine. Combination therapy with lamivudine plus zidovudine delayed the emergence of substitutions conferring resistance to zidovudine.

Cross-Resistance: Cross-resistance has been observed among NRTIs.

Abacavir: Isolates containing abacavir resistance-associated amino acid substitutions, namely, K65R, L74V, Y115F, and M184V, exhibited cross-resistance to didanosine, emtricitabine, lamivudine, tenofovir, and zalcitabine in cell culture and in subjects. The K65R substitution can confer resistance to abacavir, didanosine, emtricitabine, lamivudine, stavudine, tenofovir, and zalcitabine; the L74V substitution can confer resistance to abacavir, didanosine, and zalcitabine; and the M184V substitution can confer resistance to abacavir, didanosine, emtricitabine, lamivudine, and zalcitabine. An increasing number of thymidine analogue mutations (TAMs: M41L, D67N, K70R, L210W, T215Y/F, K219E/R/H/Q/N) is associated with a progressive reduction in abacavir susceptibility.

Lamivudine: Cross-resistance to abacavir, didanosine, tenofovir, and zalcitabine has been observed in some subjects harboring lamivudine-resistant HIV-1 isolates. In some subjects treated with zidovudine plus didanosine or zalcitabine, isolates resistant to multiple drugs, including lamivudine, have emerged (see under Zidovudine below). Cross-resistance between lamivudine and zidovudine has not been reported.

Zidovudine: In a trial of 167 HIV-infected subjects, isolates (n = 2) with multi-drug resistance to didanosine, lamivudine, stavudine, zalcitabine, and zidovudine were recovered from subjects treated for ≥1 year with zidovudine plus didanosine or zidovudine plus zalcitabine. The pattern of resistance-associated amino acid substitutions with such combination therapies was different (A62V, V75I, F77L, F116Y, Q151M) from the pattern with zidovudine monotherapy, with the Q151M substitution being most commonly associated with multi-drug resistance. The substitution at codon 151 in combination with substitutions at 62, 75, 77, and 116 results in a virus with reduced susceptibility to didanosine, lamivudine, stavudine, zalcitabine, and zidovudine. TAMs are selected by zidovudine and confer cross-resistance to abacavir, didanosine, stavudine, tenofovir, and zalcitabine.

13 NONCLINICAL TOXICOLOGY

13.1 Carcinogenesis, Mutagenesis, Impairment of Fertility

Carcinogenicity:

Abacavir: Abacavir was administered orally at 3 dosage levels to separate groups of mice and rats in 2-year carcinogenicity studies. Results showed an increase in the incidence of malignant and non-malignant tumors. Malignant tumors occurred in the preputial gland of males and the clitoral gland of females of both species, and in the liver of female rats. In addition, non-malignant tumors also occurred in the liver and thyroid gland of female rats. These observations were made at systemic exposures in the range of 6 to 32 times the human exposure at the recommended dose. It is not known how predictive the results of rodent carcinogenicity studies may be for humans.

Lamivudine: Long-term carcinogenicity studies with lamivudine in mice and rats showed no evidence of carcinogenic potential at exposures up to 10 times (mice) and 58 times (rats) those observed in humans at the recommended therapeutic dose for HIV-1 infection.

Zidovudine: Zidovudine was administered orally at 3 dosage levels to separate groups of mice and rats (60 females and 60 males in each group). Initial single daily doses were 30, 60, and 120 mg/kg/day in mice and 80, 220, and 600 mg/kg/day in rats. The doses in mice were reduced to 20, 30, and 40 mg/kg/day after day 90 because of treatment-related anemia, whereas in rats only the high dose was reduced to 450 mg/kg per day on day 91 and then to 300 mg/kg/day on day 279.

In mice, 7 late-appearing (after 19 months) vaginal neoplasms (5 nonmetastasizing squamous cell carcinomas, 1 squamous cell papilloma, and 1 squamous polyp) occurred in animals given the highest dose. One late-appearing squamous cell papilloma occurred in the vagina of a middle-dose animal. No vaginal tumors were found at the lowest dose.

In rats, 2 late-appearing (after 20 months), nonmetastasizing vaginal squamous cell carcinomas occurred in animals given the highest dose. No vaginal tumors occurred at the low or middle dose in rats. No other drug-related tumors were observed in either sex of either species.

At doses that produced tumors in mice and rats, the estimated drug exposure (as measured by AUC) was approximately 3 times (mouse) and 24 times (rat) the estimated human exposure at the recommended therapeutic dose of 100 mg every 4 hours.

Two transplacental carcinogenicity studies were conducted in mice. One study administered zidovudine at doses of 20 mg/kg/day or 40 mg/kg/day from gestation day 10 through parturition and lactation with dosing continuing in offspring for 24 months postnatally. At these doses, exposures were approximately 3 times the estimated human exposure at the recommended doses. After 24 months at the 40-mg/kg/day dose, an increase in incidence of vaginal tumors was noted with no increase in tumors in the liver or lung or any other organ in either gender. These findings are consistent with results of the standard oral carcinogenicity study in mice, as described earlier. A second study administered zidovudine at maximum tolerated doses of 12.5 mg/day or 25 mg/day (~1,000 mg/kg nonpregnant body weight or ~450 mg/kg of term body weight) to pregnant mice from days 12 through 18 of gestation. There was an increase in the number of tumors in the lung, liver, and female reproductive tracts in the offspring of mice receiving the higher dose level of zidovudine.

It is not known how predictive the results of rodent carcinogenicity studies may be for humans.

Mutagenicity:

Abacavir: Abacavir induced chromosomal aberrations both in the presence and absence of metabolic activation in an in vitro cytogenetic study in human lymphocytes. Abacavir was mutagenic in the absence of metabolic activation, although it was not mutagenic in the presence of metabolic activation in an L5178Y/TK+/- mouse lymphoma assay. Abacavir was clastogenic in males and not clastogenic in females in an in vivo mouse bone marrow micronucleus assay. Abacavir was not mutagenic in bacterial mutagenicity assays in the presence and absence of metabolic activation.

Lamivudine: Lamivudine was mutagenic in an L5178Y/TK+/- mouse lymphoma assay and clastogenic in a cytogenetic assay using cultured human lymphocytes. Lamivudine was negative in a microbial mutagenicity assay, in an in vitro cell transformation assay, in a rat micronucleus test, in a rat bone marrow cytogenetic assay, and in an assay for unscheduled DNA synthesis in rat liver.

Zidovudine: Zidovudine was mutagenic in an L5178Y/TK+/- mouse lymphoma assay, positive in an in vitro cell transformation assay, clastogenic in a cytogenetic assay using cultured human lymphocytes, and positive in mouse and rat micronucleus tests after repeated doses. It was negative in a cytogenetic study in rats given a single dose.

Impairment of Fertility:

Abacavir: Abacavir had no adverse effects on the mating performance or fertility of male and female rats at a dose approximately 8 times the human exposure at the recommended dose based on body surface area comparisons.

Lamivudine: In a study of reproductive performance, lamivudine, administered to male and female rats at doses up to 130 times the usual adult dose based on body surface area considerations, revealed no evidence of impaired fertility judged by conception rates and no effect on the survival, growth, and development to weaning of the offspring.

Zidovudine: Zidovudine, administered to male and female rats at doses up to 7 times the usual adult dose based on body surface area considerations, had no effect on fertility judged by conception rates.

13.2 Animal Toxicology and/or Pharmacology

Myocardial degeneration was found in mice and rats following administration of abacavir for 2 years. The systemic exposures were equivalent to 7 to 24 times the expected systemic exposure in humans. The clinical relevance of this finding has not been determined.

14 CLINICAL STUDIES

The following trial was conducted with the individual components of TRIZIVIR [see Clinical Pharmacology (12.3)].

CNA3005 was a multicenter, double-blind, controlled trial in which 562 HIV-1-infected, therapy-naive adults were randomized to receive either ZIAGEN (300 mg twice daily) plus COMBIVIR (lamivudine 150 mg/zidovudine 300 mg twice daily), or indinavir (800 mg 3 times a day) plus COMBIVIR twice daily. The trial was stratified at randomization by pre-entry plasma HIV-1 RNA 10,000 to 100,000 copies/mL and plasma HIV-1 RNA >100,000 copies/mL. Trial participants were male (87%), Caucasian (73%), black (15%), and Hispanic (9%). At baseline the median age was 36 years, the median pretreatment CD4+ cell count was 360 cells/mm^3, and median plasma HIV-1 RNA was 4.8 log10 copies/mL. Proportions of subjects with plasma HIV-1 RNA <400 copies/mL (using Roche AMPLICOR HIV-1 MONITOR® Test) through 48 weeks of treatment are summarized in Table 5.

Table 5. Outcomes of Randomized Treatment Through Week 48 (CNA3005)
Outcome | ZIAGEN plus; Lamivudine/Zidovudine; (n = 262) | Indinavir plus; Lamivudine/Zidovudine; (n = 265)
Respondera | 49% | 50%
Virologic failureb | 31% | 28%
Discontinued due to adverse reactions | 10% | 12%
Discontinued due to other reasonsc | 11% | 10%
a Patients achieved and maintained confirmed HIV-1 RNA <400 copies/mL.
b Includes viral rebound and failure to achieve confirmed <400 copies/mL by Week 48.
c Includes consent withdrawn, lost to follow-up, protocol violations, those with missing data, clinical progression, and other.

Treatment response by plasma HIV-1 RNA strata is shown in Table 6.

Table 6. Proportions of Responders Through Week 48 By Screening Plasma HIV-1 RNA Levels (CNA3005)
Screening; HIV-1 RNA; (copies/mL) | ZIAGEN plus; Lamivudine/Zidovudine; (n = 262) |  | Indinavir plus; Lamivudine/Zidovudine; (n = 265)
Screening; HIV-1 RNA; (copies/mL) | <400 copies/mL | n | <400 copies/mL | N
≥10,000 - ≤100,000 | 50% | 166 | 48% | 165
>100,000 | 48% | 96 | 52% | 100

In subjects with baseline viral load >100,000 copies/mL, percentages of subjects with HIV-1 RNA levels <50 copies/mL were 31% in the group receiving abacavir vs. 45% in the group receiving indinavir.

Through Week 48, an overall mean increase in CD4+ cell count of about 150 cells/mm^3 was observed in both treatment arms. Through Week 48, 9 subjects (3.4%) in the group receiving abacavir sulfate (6 CDC classification C events and 3 deaths) and 3 subjects (1.5%) in the group receiving indinavir (2 CDC classification C events and 1 death) experienced clinical disease progression.

15 REFERENCES

1. Data Collection on Adverse Events of Anti-HIV Drugs (D:A:D) Study Group. Lancet. 2008;371 (9622):1417-1426.

16 HOW SUPPLIED/STORAGE AND HANDLING

TRIZIVIR is available as tablets. Each tablet contains 300 mg of abacavir as abacavir sulfate, 150 mg of lamivudine, and 300 mg of zidovudine. The tablets are blue-green capsule-shaped, film-coated, and imprinted with GX LL1 on one side with no markings on the reverse side.

They are supplied by State of Florida DOH Central Pharmacy as follows:

NDC | Strength | Quantity/Form | Color | Source Prod. Code
53808-0990-1 | 300 mg / 150 mg / 300 mg | 30 Tablets in a Blister Pack | blue-green | 49702-217

Store at 25°C (77°F); excursions permitted to 15° to 30°C (59° to 86°F) (see USP Controlled Room Temperature).

17 PATIENT COUNSELING INFORMATION

See FDA-approved patient labeling (Medication Guide)

Hypersensitivity Reaction: Inform patients:

- that a Medication Guide and Warning Card summarizing the symptoms of the abacavir hypersensitivity reaction and other product information will be dispensed by the pharmacist with each new prescription and refill of TRIZIVIR, and encourage the patient to read the Medication Guide and Warning Card every time to obtain any new information that may be present about TRIZIVIR. (The complete text of the Medication Guide is reprinted at the end of this document.)
- to carry the Warning Card with them.
- how to identify a hypersensitivity reaction[see Warnings and Precautions (5.1), Medication Guide].
- that if they develop symptoms consistent with a hypersensitivity reaction they should call their doctor right away to determine if they should stop taking TRIZIVIR.
- that a hypersensitivity reaction can worsen and lead to hospitalization or death if TRIZIVIR is not immediately discontinued.
- to not restart TRIZIVIR or any other abacavir-containing product following a hypersensitivity reaction because more severe symptoms can occur within hours and may include life-threatening hypotension and death.
- that a hypersensitivity reaction is usually reversible if it is detected promptly and TRIZIVIR is stopped right away.
- that if they have interrupted TRIZIVIR for reasons other than symptoms of hypersensitivity (for example, those who have an interruption in drug supply), a serious or fatal hypersensitivity reaction may occur with reintroduction of abacavir.
- to not restart TRIZIVIR or any other abacavir-containing product without medical consultation and that restarting abacavir needs to be undertaken only if medical care can be readily accessed by the patient or others.
- TRIZIVIR should not be coadministered with ATRIPLA, COMBIVIR, COMPLERA, EMTRIVA, EPIVIR, EPIVIR-HBV, EPZICOM, RETROVIR (zidovudine), TRUVADA, or ZIAGEN.

Neutropenia and Anemia: Patients should be informed that the important toxicities associated with zidovudine are neutropenia and/or anemia. They should be told of the extreme importance of having their blood counts followed closely while on therapy, especially for patients with advanced HIV-1 disease [see Warnings and Precautions (5.2)].

Myopathy: Patients should be informed that myopathy and myositis with pathological changes, similar to that produced by HIV-1 disease, have been associated with prolonged use of zidovudine [see Warnings and Precautions (5.3)].

Lactic Acidosis/Hepatomegaly: Inform patients that some HIV medicines, including TRIZIVIR, can cause a rare, but serious condition called lactic acidosis with liver enlargement (hepatomegaly) [see Warnings and Precautions (5.4)].

HIV-1/ HBV Co-Infection: Patients co-infected with HIV-1 and HBV should be informed that deterioration of liver disease has occurred in some cases when treatment with lamivudine was discontinued. Patients should be advised to discuss any changes in regimen with their physician [see Warnings and Precautions (5.5)].

HIV-1/HCV Co-Infection: Patients with HIV-1/HCV co-infection should be informed that hepatic decompensation (some fatal) has occurred in HIV-1/HCV co-infected patients receiving combination antiretroviral therapy for HIV-1 and interferon alfa with or without ribavirin [see Warnings and Precautions (5.6)].

Redistribution/Accumulation of Body Fat: Inform patients that redistribution or accumulation of body fat may occur in patients receiving antiretroviral therapy and that the cause and long-term health effects of these conditions are not known at this time [see Warnings and Precautions (5.8)].

Information About HIV-1 Infection: TRIZIVIR is not a cure for HIV-1 infection and patients may continue to experience illnesses associated with HIV-1 infection, including opportunistic infections. Patients should remain under the care of a physician when using TRIZIVIR.

Patients should be advised to avoid doing things that can spread HIV-1 infection to others.

- Do not share needles or other injection equipment.
- Do not share personal items that can have blood or body fluids on them, like toothbrushes and razor blades.
- Do not have any kind of sex without protection. Always practice safe sex by using a latex or polyurethane condom to lower the chance of sexual contact with semen, vaginal secretions, or blood.
- Do not breastfeed. Lamivudine and zidovudine are excreted in human breast milk. It is not known if abacavir can be passed to your baby in your breast milk and whether it could harm your baby. Also, mothers with HIV-1 should not breastfeed because HIV-1 can be passed to the baby in the breast milk.

Patients should be informed to take all HIV medications exactly as prescribed.

COMBIVIR, EPIVIR, EPZICOM, RETROVIR, TRIZIVIR, and ZIAGEN are registered trademarks of ViiV Healthcare.

Other brands are trademarks of their respective owners and are not trademarks of ViiV Healthcare. The makers of these brands are not affiliated with and do not endorse ViiV Healthcare or its products.

Manufactured for:

ViiV Healthcare

Research Triangle Park, NC 27709

by:

GlaxoSmithKline

Research Triangle Park, NC 27709

Lamivudine is manufactured under agreement from

Shire Pharmaceuticals Group plc

Basingstoke, UK

©2013, ViiV Healthcare. All rights reserved.

This Product was Repackaged By:

State of Florida DOH Central Pharmacy
104-2 Hamilton Park Drive
Tallahassee, FL 32304
United States

MEDICATION GUIDE

TRIZIVIR® (TRY-zih-veer)

(abacavir sulfate, lamivudine, and zidovudine

Tablets

Read this Medication Guide before you start taking TRIZIVIR and each time you get a refill. There may be new information. This information does not take the place of talking to your healthcare provider about your medical condition or your treatment. Be sure to carry your TRIZIVIR Warning Card with you at all times.

What is the most important information I should know about TRIZIVIR?

1.Serious allergic reaction (hypersensitivity reaction). TRIZIVIR contains abacavir (also contained in ZIAGEN® and EPZICOM®). Patients taking TRIZIVIR may have a serious allergic reaction (hypersensitivity reaction) that can cause death. Your risk of this allergic reaction is much higher if you have a gene variation called HLA-B*5701. Your healthcare provider can determine with a blood test if you have this gene variation.

If you get a symptom from 2 or more of the following groups while taking TRIZIVIR, call your healthcare provider right away to find out if you should stop taking TRIZIVIR.

 | Symptom(s)
Group 1 | Fever
Group 2 | Rash
Group 3 | Nausea, vomiting, diarrhea, abdominal (stomach area) pain
Group 4 | Generally ill feeling, extreme tiredness, or achiness
Group 5 | Shortness of breath, cough, sore throat

A list of these symptoms is on the Warning Card your pharmacist gives you. Carry this Warning Card with you at all times.

If you stop TRIZIVIR because of an allergic reaction, never take TRIZIVIR(abacavir sulfate, lamivudine, and zidovudine)or any other abacavir-containing medicine (ZIAGEN and EPZICOM) again. If you take TRIZIVIR or any other abacavir-containing medicine again after you have had an allergic reaction, within hours you may get life-threatening symptoms that may include very low blood pressure or death. If you stop TRIZIVIR, for any other reason, even for a few days, and you are not allergic to TRIZIVIR, talk with your healthcare provider before taking it again. Taking TRIZIVIR again can cause a serious allergic or life-threatening reaction, even if you never had an allergic reaction to it before.

If your healthcare provider tells you that you can take TRIZIVIR again, start taking it when you are around medical help or people who can call a healthcare provider if you need one.

2. Blood problems. RETROVIR®, one of the medicines in TRIZIVIR, can cause serious blood cell problems. These include reduced numbers of white blood cells (neutropenia) and extremely reduced numbers of red blood cells (anemia). These blood cell problems are especially likely to happen in patients with advanced human immunodeficiency virus (HIV) disease or AIDS. Your doctor should be checking your blood cell counts regularly while you are taking TRIZIVIR. This is especially important if you have advanced HIV or AIDS. This is to make sure that any blood cell problems are found quickly.

3. Lactic Acidosis (buildup of acid in the blood). Some human immunodeficiency virus (HIV) medicines, including TRIZIVIR, can cause a rare but serious condition called lactic acidosis. Lactic acidosis is a serious medical emergency that can cause death and must be treated in the hospital.

Call your healthcare provider right away if you get any of the following signs or symptoms of lactic acidosis:

- you feel very weak or tired
- you have unusual (not normal) muscle pain
- you have trouble breathing
- you have stomach pain with nausea and vomiting
- you feel cold, especially in your arms and legs
- you feel dizzy or light-headed
- you have a fast or irregular heartbeat

4. Serious liver problems. Some people who have taken medicines like TRIZIVIR have developed serious liver problems called hepatotoxicity, with liver enlargement (hepatomegaly) and fat in the liver (steatosis). Hepatomegaly with steatosis is a serious medical emergency that can cause death.

Call your healthcare provider right away if you get any of the following signs or symptoms of liver problems:

- your skin or the white part of your eyes turns yellow (jaundice)
- your urine turns dark
- your bowel movements (stools) turn light in color
- you don’t feel like eating food for several days or longer
- you feel sick to your stomach (nausea)
- you have lower stomach area (abdominal) pain

You may be more likely to get lactic acidosis or serious liver problems if you are female, very overweight, or have been taking nucleoside analogue medicines for a long time.

5. Use with interferon and ribavirin-based regimens. Worsening of liver disease (sometimes resulting in death) has occurred in patients infected with both HIV and hepatitis C virus who are taking anti-HIV medicines and are also being treated for hepatitis C with interferon with or without ribavirin. If you are taking TRIZIVIR as well as interferon with or without ribavirin and you experience side effects, be sure to tell your healthcare provider.

6. If you have HIV and hepatitis B virus infection, your hepatitis B virus infection may get worse if you stop taking TRIZIVIR.

- Take TRIZIVIR exactly as prescribed.
- Do not run out of TRIZIVIR.
- Do not stop TRIZIVIR without talking to your healthcare provider.

Your healthcare provider should monitor your health and do regular blood tests to check your liver if you stop taking TRIZIVIR.

7. Muscle weakness (myopathy). RETROVIR, one of the medicines in TRIZIVIR, can cause muscle weakness. This can be a serious problem.

What is TRIZIVIR?

TRIZIVIR is a prescription medicine used to treat HIV infection. TRIZIVIR contains 3 medicines: abacavir (ZIAGEN), lamivudine or 3TC (EPIVIR®), and zidovudine, AZT, or ZDV (RETROVIR). All 3 of these medicines are called nucleoside analogue reverse transcriptase inhibitors (NRTIs). When used together, they help lower the amount of HIV in your blood.

- TRIZIVIR does not cure HIV infection or AIDS.
- It is not known if TRIZIVIR will help you live longer or have fewer of the medical problems that people get with HIV or AIDS.
- It is very important that you see your healthcare provider regularly while you are taking TRIZIVIR.

Who should not take TRIZIVIR?

Do not take TRIZIVIR if you:

- are allergic to abacavir or any of the ingredients in TRIZIVIR. See the end of this Medication Guide for a complete list of ingredients in TRIZIVIR.
- have certain liver problems.
- are an adolescent who weighs less than 90 pounds.

What should I tell my healthcare provider before taking TRIZIVIR?

Before you take TRIZIVIR, tell your healthcare provider if you:

- have been tested and know whether or not you have a particular gene variation called HLA-B*5701.
- have hepatitis B virus infection or have other liver problems.
- have kidney problems.
- have low blood cell counts (bone marrow problem). Ask your doctor if you are not sure.
- have heart problems, smoke, or have diseases that increase your risk of heart disease such as high blood pressure, high cholesterol, or diabetes.
- are pregnant or plan to become pregnant. It is not known if TRIZIVIR will harm your unborn baby. Talk to your healthcare provider if you are pregnant or plan to become pregnant.

Pregnancy Registry. If you take TRIZIVIR while you are pregnant, talk to your healthcare provider about how you can take part in the Pregnancy Registry for TRIZIVIR. The purpose of the pregnancy registry is to collect information about the health of you and your baby.

- are breastfeeding or plan to breastfeed. Do not breastfeed. Lamivudine and zidovudine are excreted in human breast milk. We do not know if abacavir can be passed to your baby in your breast milk and whether it could harm your baby. Also, mothers with HIV-1 should not breastfeed because HIV-1 can be passed to the baby in the breast milk.

Tell your healthcare provider about all the medicines you take, including prescription and nonprescription medicines, vitamins, and herbal supplements.

Especially tell your healthcare provider if you take:

- alcohol
- medicines used to treat hepatitis viruses such as interferon or ribavirin
- methadone
- BACTRIM®, SEPTRA® (trimethoprim [TMP/sulfamethoxazole SMX])
- CYTOVENE®, DHPG (ganciclovir)
- interferon-alfa
- ADRIAMYCIN® (doxorubicin)
- COPEGUS®, REBETOL®, VIRAZOLE® (ribavirin)
- any bone marrow suppressive medicines or cytotoxic medicines. Ask your doctor if you are not sure.
- ATRIPLA® (efavirenz/emtricitabine/tenofovir disoproxil fumarate)
- COMBIVIR® (lamivudine and zidovudine)
- COMPLERA® (emtricitabine/rilpivirine/tenofovir disoproxil fumarate)
- EMTRIVA® (emtricitabine)
- EPIVIR or EPIVIR-HBV® (lamivudine)
- EPZICOM (abacavir sulfate and lamivudine)
- RETROVIR (zidovudine)
- TRUVADA® (emtricitabine/tenofovir disoproxil fumarate)
- ZERIT® (stavudine)
- ZIAGEN (abacavir sulfate)

Ask your healthcare provider if you are not sure if you take one of the medicines listed above.

TRIZIVIR may affect the way other medicines work, and other medicines may affect how TRIZIVIR works.

Know the medicines you take. Keep a list of your medicines with you to show to your healthcare provider and pharmacist when you get a new medicine.

How should I take TRIZIVIR?

- Take TRIZIVIR exactly as your healthcare provider tells you to take it.
- TRIZIVIR may be taken with or without food.
- Do not skip doses.
- Do not let your TRIZIVIR run out.

If you stop your anti-HIV medicines, even for a short time, the amount of virus in your blood may increase and the virus may become harder to treat.If you take too much TRIZIVIR, call your healthcare provider or poison control center or go to the nearest hospital emergency room right away.

What are the possible side effects of TRIZIVIR?

TRIZIVIR can cause serious side effects including allergic reactions, lactic acidosis, and liver problems. See “What is the most important information I should know about TRIZIVIR?”

- Blood problems.
- Muscle weakness.
- Changes in immune system (Immune Reconstitution Syndrome). Your immune system may get stronger and begin to fight infections that have been hidden in your body for a long time. Tell your healthcare provider if you start having new or worse symptoms of infection after you start taking TRIZIVIR.
- Changes in body fat (fat redistribution). Changes in body fat (lipoatrophy or lipodystrophy) can happen in some people taking antiretroviral medicines including TRIZIVIR.
These changes may include:

- more fat in or around your trunk, upper back and neck (buffalo hump), breast or chest
- loss of fat in your legs, arms, or face
- Heart attack (myocardial infarction). Some HIV medicines including TRIZIVIR may increase your risk of heart attack.

The most common side effects of TRIZIVIR include:

- nausea
- headache
- weakness or tiredness
- vomiting
- diarrhea
- fever and/or chills
- depression
- muscle and joint pain
- skin rashes
- ear, nose, throat infections
- cold symptoms
- nervousness

Tell your healthcare provider if you have any side effect that bothers you or that does not go away.

These are not all the possible side effects of TRIZIVIR. For more information, ask your healthcare provider or pharmacist.

Call your doctor for medical advice about side effects. You may report side effects to FDA at 1-800-FDA-1088.

How should I store TRIZIVIR?

- Store TRIZIVIR at 59°F to 86°F (15°C to 30°C).
- Keep TRIZIVIR and all medicines out of the reach of children.

General information for safe and effective use of TRIZIVIR.

Avoid doing things that can spread HIV-1 infection to others.

- Do not share needles or other injection equipment.
- Do not share personal items that can have blood or body fluids on them, like toothbrushes and razor blades.
- Do not have any kind of sex without protection. Always practice safe sex by using a latex or polyurethane condom to lower the chance of sexual contact with semen, vaginal secretions, or blood.

Medicines are sometimes prescribed for purposes other than those listed in a Medication Guide. Do not use TRIZIVIR for a condition for which it was not prescribed. Do not give TRIZIVIR to other people, even if they have the same symptoms that you have. It may harm them.

This Medication Guide summarizes the most important information about TRIZIVIR. If you would like more information, talk with your healthcare provider. You can ask your healthcare provider or pharmacist for the information about TRIZIVIR that is written for healthcare professionals.

For more information go to www.TRIZIVIR.com or call 1-877-844-8872.

What are the ingredients in TRIZIVIR?

Active ingredients: abacavir sulfate, lamivudine, and zidovudine

Inactive ingredients: magnesium stearate, microcrystalline cellulose, sodium starch glycolate, and OPADRY® green 03B11434, a film coating made of FD&C Blue No. 2, hypromellose, polyethylene glycol, titanium dioxide, and yellow iron oxide.

This Medication Guide has been approved by the US Food and Drug Administration.

COMBIVIR, EPIVIR, EPZICOM, RETROVIR, TRIZIVIR, and ZIAGEN are registered trademarks of ViiV Healthcare.

The brands listed are trademarks of their respective owners and are not trademarks of ViiV Healthcare. The makers of these brands are not affiliated with and do not endorse ViiV Healthcare or its products.

Manufactured for:

ViiV Healthcare

Research Triangle Park, NC 27709

by:

GlaxoSmithKline

Research Triangle Park, NC 27709

Lamivudine is manufactured under agreement from

Shire Pharmaceuticals Group plc

Basingstoke, UK

©2013, ViiV Healthcare. All rights reserved.

This Product was Repackaged By:

State of Florida DOH Central Pharmacy
104-2 Hamilton Park Drive
Tallahassee, FL 32304
United States

PACKAGE LABEL

Label Image for 53808-0990
300mg / 150mg / 300mg